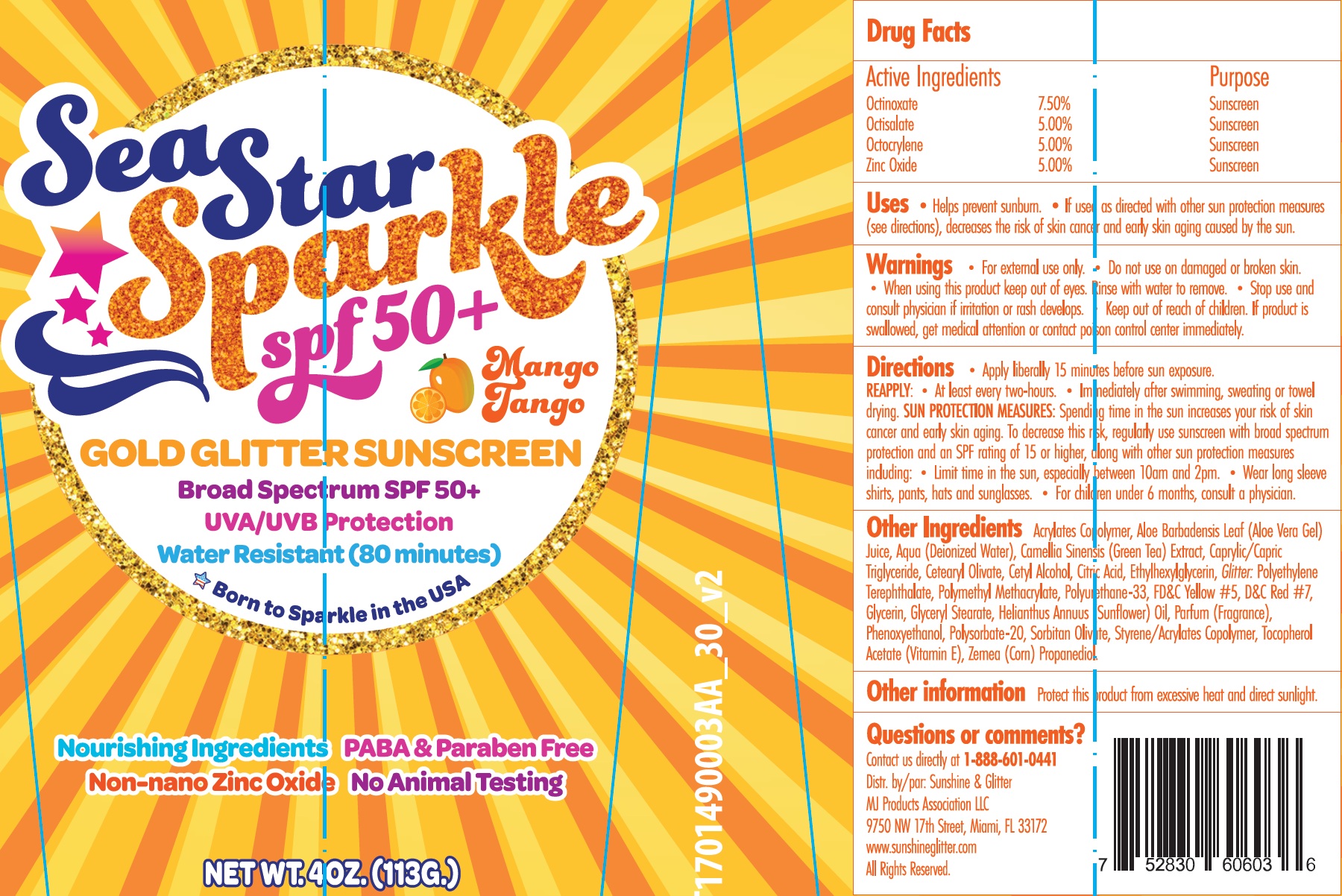 DRUG LABEL: Sea Star Sparkle SPF-50 MANGO-TANGO
NDC: 72085-147 | Form: CREAM
Manufacturer: MJ Products Association, LLC
Category: otc | Type: HUMAN OTC DRUG LABEL
Date: 20231115

ACTIVE INGREDIENTS: OCTINOXATE 75 mg/1 g; OCTISALATE 50 mg/1 g; OCTOCRYLENE 50 mg/1 g; ZINC OXIDE 50 mg/1 g
INACTIVE INGREDIENTS: BUTYL ACRYLATE/METHYL METHACRYLATE/METHACRYLIC ACID COPOLYMER (18000 MW); ALOE VERA LEAF; WATER; GREEN TEA LEAF; MEDIUM-CHAIN TRIGLYCERIDES; CETEARYL OLIVATE; CETYL ALCOHOL; CITRIC ACID MONOHYDRATE; ETHYLHEXYLGLYCERIN; POLY(METHYL METHACRYLATE; 450000 MW); FD&C YELLOW NO. 5; D&C RED NO. 7; GLYCERIN; GLYCERYL MONOSTEARATE; PHENOXYETHANOL; POLYSORBATE 20; SORBITAN OLIVATE; STYRENE

Sea Star Sparkle SPF-50 MANGO-TANGO

Active Ingredients

Octinoxate 7.50%

Octisalate 5.00%

Octocrylene 5.00%

Zinc Oxide 5.00%

Purpose

Sunscreen

Uses

- Helps prevent sunburn.
- If used as directed with other sun protection measures (see directions), decreases the risk of skin cancer and early skin aging caused by the sun.

Warnings

- For external use only

Do not use

on damaged or broken skin.

When using this product

keep out of eyes. Rinse with water to remove.

Stop use and consult physician

if irritation or rash develops.

Keep out of reach of children.

If product is swallowed, get medical attention or contact poison control center immediately.

Directions

- Apply liberally 15 minutes before sun exposure. REAPPLY:
- At least every two-hours.
- Immediately after swimming, sweating or towel drying. : Spending time in the sun increases your risk of skin cancer and early skin aging. To decrease this risk, regularly use sunscreen with broad spectrum protection and an SPF rating of 15 or higher, along with other sun protection measures including: SUN PROTECTION MEASURES
- Limit time in the sun, especially between 10am to 2pm.
- Wear long sleeve shirts, pants, hats and sunglasses.

Other Ingredients

Acrylates Copolymer, Aloe Barbadensis Leaf (Aloe Vera Gel) Juice, Aqua (Deionized Water), Camellia Sinensis (Green Tea) Extract, Caprylic/Capric Triglyceride, Cetearyl Olivate, Cetyl Alcohol, Citric Acid, Ethylhexylglycerin, : Polyethylene Terephthalate, Polymethyl Methacrylate, Polyurethane-33, FD&C Yellow #5, D&C Red #7, Glycerin, Glyceryl Stearate, Helianthus Annuus (Sunflower) Oil, Parfum (Fragrance), Phenoxyethanol, Polysorbate-20, Sorbitan Olivate, Styrene/Acrylates Copolymer, Tocopherol Acetate (Vitamin E), Zemea (Corn) Propanediol. Glitter

Other information

Protect this product from excessive heat and direct sunlight.

Questions or comments?

Contact us directly at 1-888-601-0441

Distr. by/par: Sunshine & Glitter

MJ Products Association LLC

9750 NW 17th Street, Miami, FL 33172

www.sunshineglitter.com

All Right Reserved.